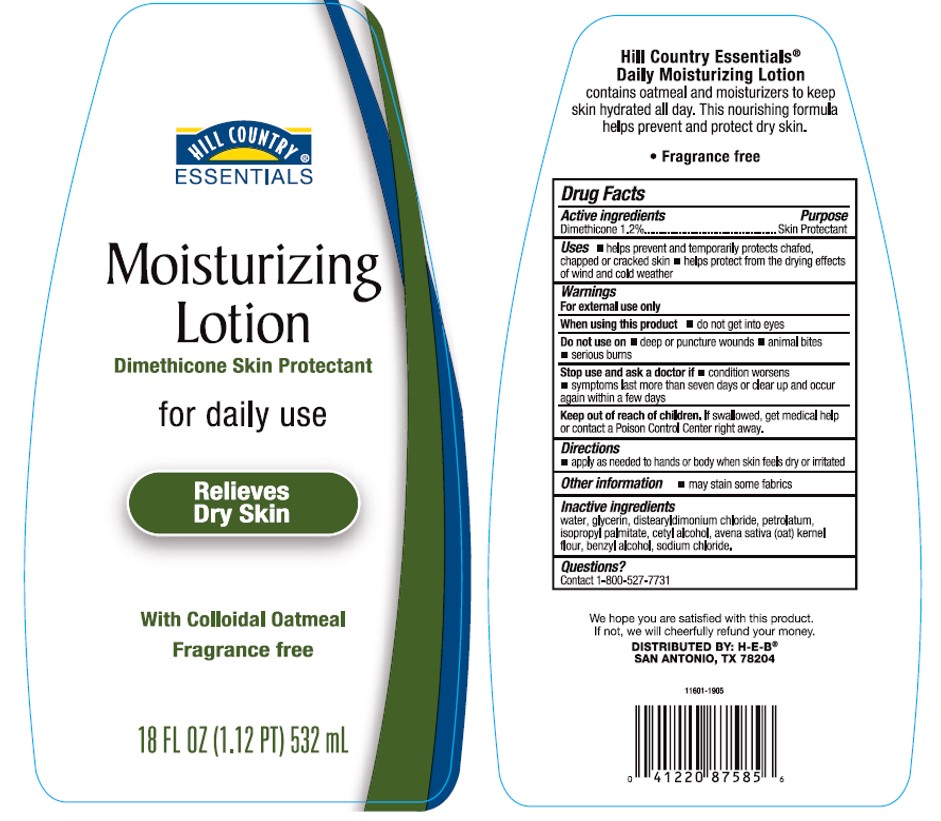 DRUG LABEL: Hill Country Essentials
NDC: 37808-995 | Form: LOTION
Manufacturer: H.E.B
Category: otc | Type: HUMAN OTC DRUG LABEL
Date: 20241015

ACTIVE INGREDIENTS: DIMETHICONE 12 mg/1 mL
INACTIVE INGREDIENTS: WATER; GLYCERIN; DISTEARYLDIMONIUM CHLORIDE; PETROLATUM; ISOPROPYL PALMITATE; CETYL ALCOHOL; OATMEAL; BENZYL ALCOHOL; SODIUM CHLORIDE

Hill Country Essentials Moisturizing Lotion

Active ingredients

Dimethicone 1.2%

Purpose

Skin Protectant

Uses

- helps prevent sunburn
- if used as directed with other sun protection measures (see Directions), decreases the risk of skin cancer and early skin aging caused by the sun

Warnings

For external use only

Do not use

• deep or puncture wounds • animal bites • serious burns

When using this product

• keep out of eyes. Rinse with water to remove.

Stop use and ask a doctor if

• condition worsens • symptoms last more than seven days or clear up and occur again within a few days

Keep out of reach of children.

If swallowed, get medical help or contact a Poison Control Center right away.

Directions

- apply as needed to hands or body when skin feels dry or irritated

Other information

- may stain some fabrics

Inactive ingredients

water, glycerin, distearyldimonium chloride, petrolatum, isopropyl palmitate, cetyl alcohol, avena sativa (oat) kernel flour, benzyl alcohol, sodium chloride.